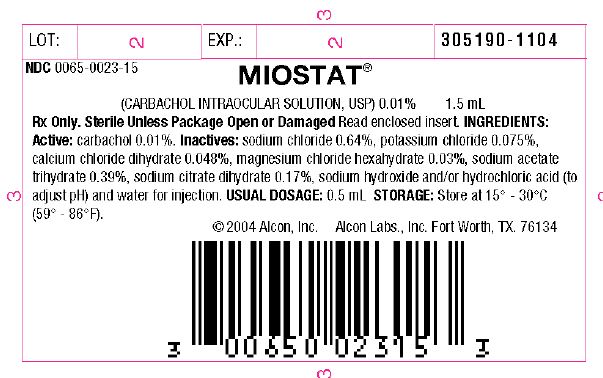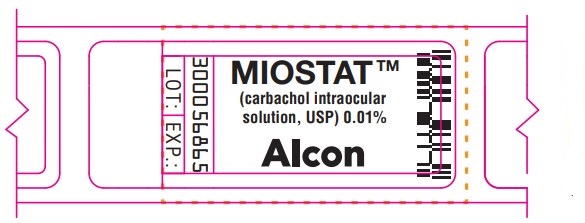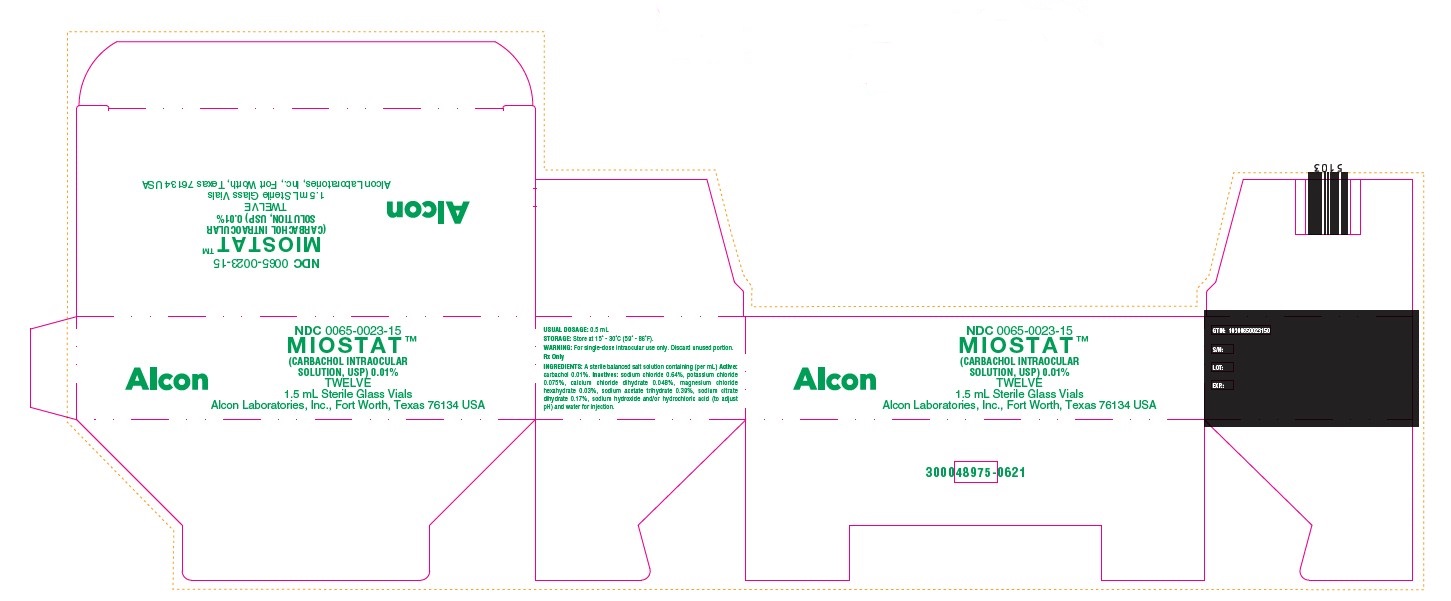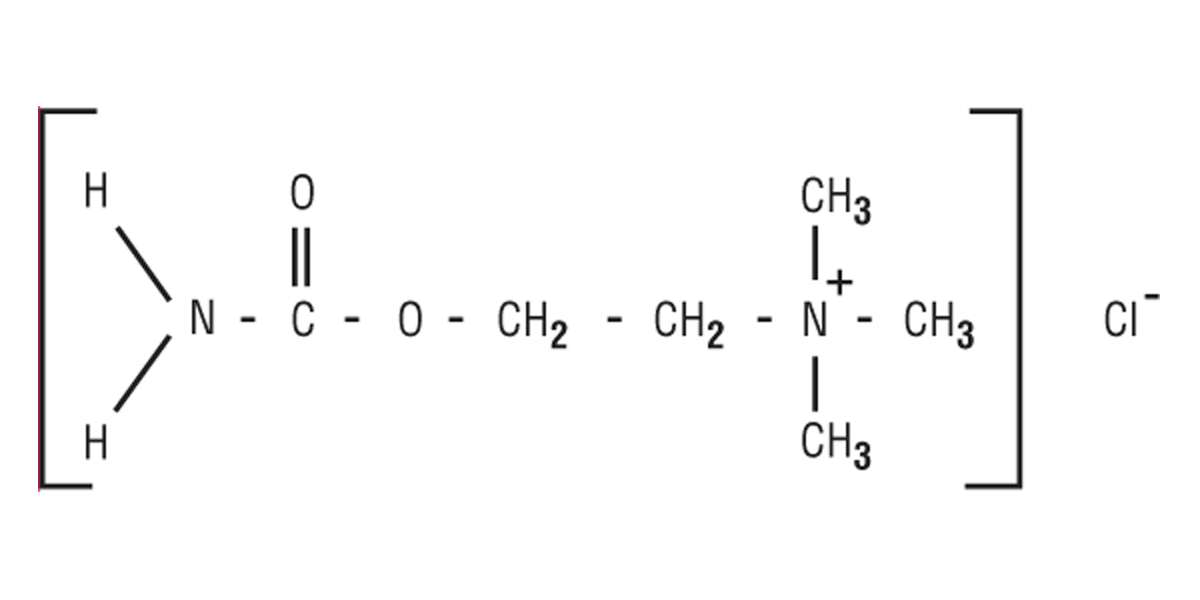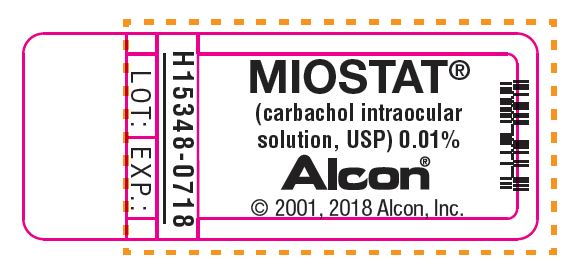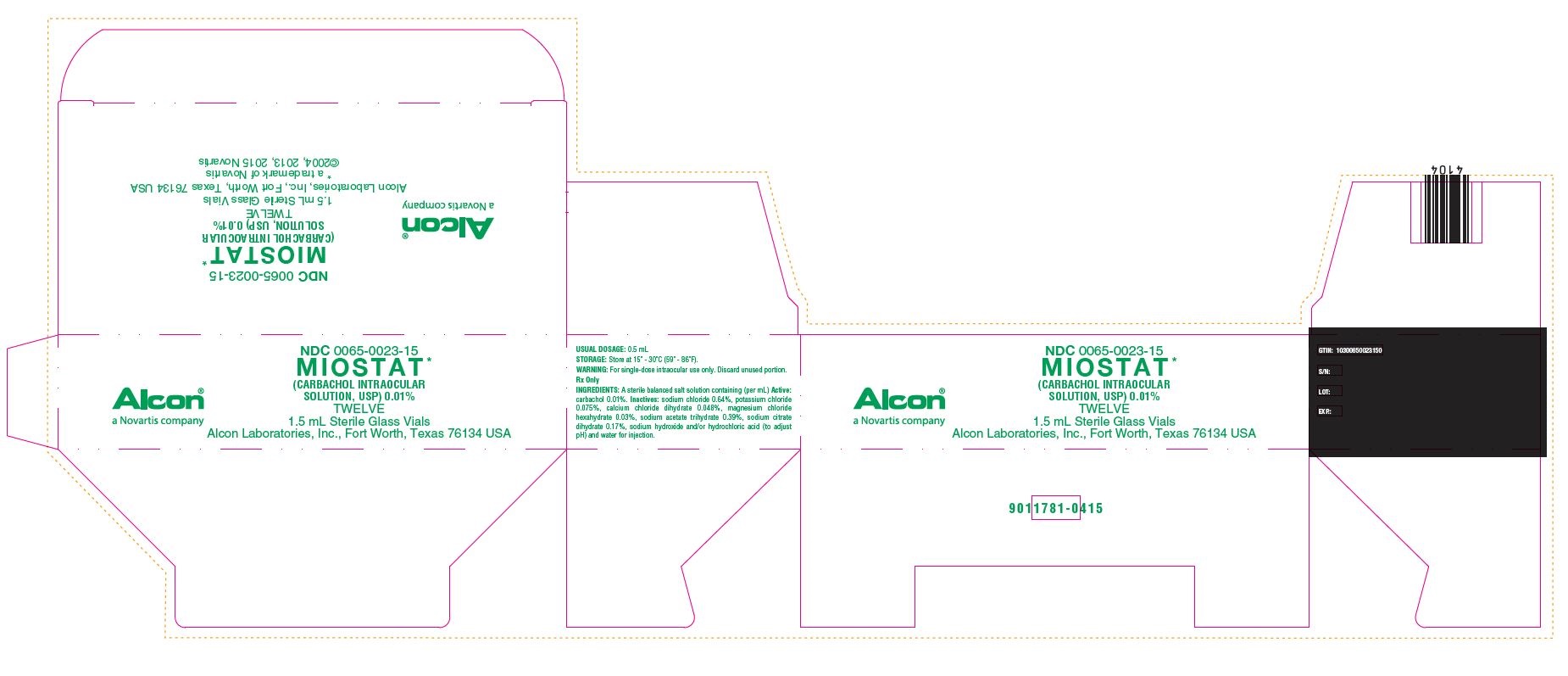 DRUG LABEL: MIOSTAT 
NDC: 0065-0023 | Form: SOLUTION
Manufacturer: Alcon Laboratories, Inc.
Category: prescription | Type: HUMAN PRESCRIPTION DRUG LABEL
Date: 20230210

ACTIVE INGREDIENTS: CARBACHOL 0.1 mg/1 mL
INACTIVE INGREDIENTS: SODIUM CHLORIDE; POTASSIUM CHLORIDE; CALCIUM CHLORIDE; MAGNESIUM CHLORIDE; SODIUM ACETATE; TRISODIUM CITRATE DIHYDRATE; SODIUM HYDROXIDE; HYDROCHLORIC ACID; WATER

MIOSTAT™
(CARBACHOL INTRAOCULAR SOLUTION, USP) 0.01%

DESCRIPTION:

MIOSTAT™ (carbachol intraocular solution, USP) 0.01% is a sterile balanced salt solution of carbachol for intraocular injection. The active ingredient is represented by the chemical structure:

Established Name: Carbachol
Chemical Name: Ethanaminium, 2-[(aminocarbonyl)oxy]-N,N,Ntrimethyl-, chloride.
Molecular Formula: C6H15CIN2O2
Molecular Weight: 182.65

Each mL of MIOSTAT™ (carbachol intraocular solution, USP) 0.01% contains: Active: carbachol 0.01%.
Inactives: sodium chloride 0.64%, potassium chloride 0.075%, calcium chloride dehydrate 0.048%, magnesium chloride hexahydrate 0.03%, sodium acetate trihydrate 0.39%, sodium citrate dihydrate 0.17%, sodium hydroxide and/or hydrochloric acid (to adjust pH) and Water for Injection. pH range is 6.5-7.5.

CLINICAL PHARMACOLOGY:

Carbachol is a potent cholinergic (parasympathomimetic) agent which produces constriction of the iris and ciliary body resulting in reduction in intraocular pressure (IOP). The exact mechanism by which carbachol lowers IOP is not precisely known.

INDICATIONS AND USAGE:

Intraocular use for obtaining miosis during surgery. In addition, MIOSTAT* (carbachol intraocular solution, USP) 0.01% reduces the intensity of IOP elevation in the first 24 hours after cataract surgery.

CONTRAINDICATIONS:

Should not be used in those persons showing hypersensitivity to any of the components of this preparation.

WARNINGS:

For single-dose intraocular use only. Discard unused portion. Intraocular carbachol 0.01% should be used with caution in patients with acute cardiac failure, bronchial asthma, peptic ulcer, hyperthyroidism, G.I. spasm, urinary tract obstruction and Parkinson's disease. The vial stopper contains natural rubber (latex) which may cause severe allergic reactions.

PRECAUTIONS:

Use only if the container is undamaged.

Carcinogenesis:

Studies in animals to evaluate the carcinogenic potential have not been conducted.

Pregnancy:

There are no adequate and well-controlled studies in pregnant women. MIOSTAT* (carbachol intraocular solution, USP) 0.01% should be used during pregnancy only if the potential benefit justifies the potential risk to the fetus.

Nursing Mothers:

It is not known if this medication is excreted in breast milk. Exercise caution when administering to a nursing woman.

Pediatric Use:

Safety and efficacy in pediatric patients have not been established.

Geriatric Use:

No overall differences in safety or effectiveness have been observed between elderly and younger patients.

ADVERSE REACTIONS:

Ocular: Corneal clouding, persistent bullous keratopathy, retinal detachment and postoperative iritis following cataract extraction have been reported.

Systemic: Side effects such as flushing, sweating, epigastric distress, abdominal cramps, tightness in urinary bladder, and headache have been reported with topical or systemic application of carbachol.

The following additional reactions have been identified during post-approval use of MIOSTAT (carbachol intraocular solution, USP) 0.01% in clinical practice. Because they are reported voluntarily from a population of unknown size, estimates of frequency cannot be made. The reactions, which have been chosen for inclusion due to either their seriousness, frequency of reporting, possible causal connection to MIOSTAT, or a combination of these factors, include: corneal edema, drug effect prolonged (miosis), eye inflammation, eye pain, intraocular pressure increased, ocular hyperemia, vision blurred, visual impairment, and vomiting.

DOSAGE AND ADMINISTRATION:

Aseptically remove the sterile vial from the blister package by peeling the backing paper and dropping the vial onto a sterile tray. Withdraw the contents into a dry sterile syringe, and replace the needle with an atraumatic cannula prior to intraocular instillation. No more than one-half milliliter should be gently instilled into the anterior chamber for the production of satisfactory miosis. It may be instilled before or after securing sutures. Miosis is usually maximal within two to five minutes after application.

HOW SUPPLIED:

In a 2.0 mL glass vial with a 1.5 mL fill, grey butyl stopper and aluminum seal packaged twelve to a carton…………………………………………………………………………..NDC 0065-0023-15

STORAGE: Store at 15° - 30°C (59° - 86°F).

© 2021 Alcon Inc.

Distributed by:
Alcon Laboratories, Inc.
Fort Worth, Texas 76134

300048977-0621

PRINCIPAL DISPLAY PANEL

NDC 0065-0023-15
MIOSTAT™
(CARBACHOL INTRAOCULAR
SOLUTION, USP) 0.01%
TWELVE
1.5 mL Sterile Glass Vials
Alcon Laboratories, Inc., Fort Worth, Texas 76134 USA
Alcon
USUAL DOSAGE: 0.5 mL
STORAGE: Store at 15 - 30C (59 - 86F).
WARNING: For single-dose intraocular use only. Discard unused portion.
Rx Only
INGREDIENTS: A sterile balanced salt solution containing (per mL) Active:
carbachol 0.01%. Inactives: sodium chloride 0.64%, potassium chloride
0.075%, calcium chloride dihydrate 0.048%, magnesium chloride
hexahydrate 0.03%, sodium acetate trihydrate 0.39%, sodium citrate
dihydrate 0.17%, sodium hydroxide and/or hydrochloric acid (to adjust
pH) and water for injection.
GTIN: 10300650023150
S/N:
LOT:
EXP.:
300048975-0621

NDC 0065-0023-15
MIOSTAT*
(CARBACHOL INTRAOCULAR SOLUTION, USP) 0.01%
TWELVE
1.5 mL Sterile Glass Vials
Alcon Laboratories, Inc., Fort Worth, Texas 76134 USA
* a trademark of Novartis
©2004, 2013, 2015 Novartis
Alcon®
a Novartis company
USUAL DOSAGE: 0.5 mL
STORAGE: Store at 15 - 30C (59 - 86F).
Rx Only
INGREDIENTS: A sterile balanced salt solution containing (per mL) Active: carbachol 0.01%. Inactives: sodium chloride 0.64%, potassium chloride 0.075%, calcium chloride dihydrate 0.048%, magnesium chloride hexahydrate 0.03%, sodium acetate trihydrate 0.39%, sodium citrate dihydrate 0.17%, sodium hydroxide and/or hydrochloric acid (to adjust pH) and water for injection.
GTIN: 10300650023150
S/N
LOT:
EXP.:
9011781-0415

MIOSTAT™
(carbachol intraocular solution, USP) 0.01%
Alcon
300056865
LOT: EXP.:

MIOSTAT®
(carbachol intraocular solution, USP) 0.01%
Alcon®
© 2001, 2018 Alcon, Inc.
H15348-0718
LOT: EXP.:

LOT: EXP: 305190-1104
NDC 0065-0023-15
MIOSTAT®
(CARBACHOL INTRAOCULAR SOLUTION, USP) 0.01% 1.5mL
Rx Only. Sterile Unless Package Open or Damaged Read enclosed insert. INGREDIENTS: Active: carbachol 0.01%. Inactives: sodium chloride 0.64%, potassium chloride 0.075%, calcium chloride dihydrate 0.048%, magnesium chloride hexahydrate 0.03%, sodium acetate trihydrate 0.39%, sodium citrate dihydrate 0.17%, sodium hydroxide and/or hydrochloric acid (to adjust pH) and water for injection. USUAL DOSAGE: 0.5mL STORAGE: Store at 15° - 30°C (59° - 86°F).
©2004 Alcon, Inc. Alcon Labs., Inc. Fort Worth, TX. 76134